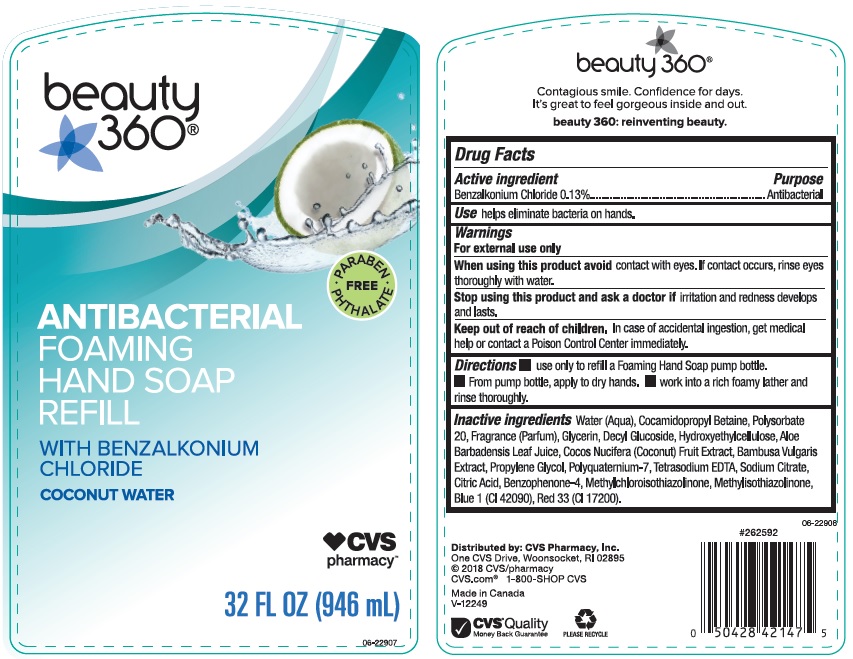 DRUG LABEL: CVS Pharmacy
NDC: 59779-842 | Form: LIQUID
Manufacturer: CVS Pharmacy
Category: otc | Type: HUMAN OTC DRUG LABEL
Date: 20200318

ACTIVE INGREDIENTS: BENZALKONIUM CHLORIDE 1.3 mg/1 mL
INACTIVE INGREDIENTS: WATER; COCAMIDOPROPYL BETAINE; POLYSORBATE 20; GLYCERIN; DECYL GLUCOSIDE; HYPROMELLOSES; ALOE VERA LEAF; COCONUT; BAMBUSA VULGARIS TOP; PROPYLENE GLYCOL; POLYQUATERNIUM-7 (70/30 ACRYLAMIDE/DADMAC; 1600000 MW); EDETATE SODIUM; SODIUM CITRATE; CITRIC ACID MONOHYDRATE; SULISOBENZONE; METHYLCHLOROISOTHIAZOLINONE; METHYLISOTHIAZOLINONE; FD&C BLUE NO. 1; D&C RED NO. 33

Drug Facts

Active ingredient

Benzalkonium Chloride 0.13%

Purpose

Antibacterial

Use

helps eliminate bacteria on hands.

Warnings

For external use only

When using this product avoid

contact with eyes. If contact occurs, rinse eyes thoroughly with water.

Stop using this product and ask a doctor if

irritation and redness develops and lasts.

Keep out of reach of children.

In case of accidental ingestion, get medical help or contact a Poison Control Center immediately.

Directions

- use only to refill a Foaming Hand Soap pump bottle.
- From pump bottle, apply to dry hands.
- Work into a rich foamy lather and rinse thoroughly.

Inactive ingredients

Water (Aqua), Cocamidopropyl Betaine, Polysorbate 20, Fragrance (Parfum), Glycerin, Decyl Glucoside, Hydroxyethylcellulose, Aloe Barbadensis Leaf Juice, Cocos Nucifera (Coconut) Fruit Extract, Bambusa Vulgaris Extract, Propylene Glycol, Polyquaternium-7, Tetrasodium EDTA, Sodium Citrate, Citric Acid, Benzophenone-4, Methylchloroisothiazolinone, Methylisothiazolinone, Blue 1 (CI 42090), Red 33 (CI 17200).